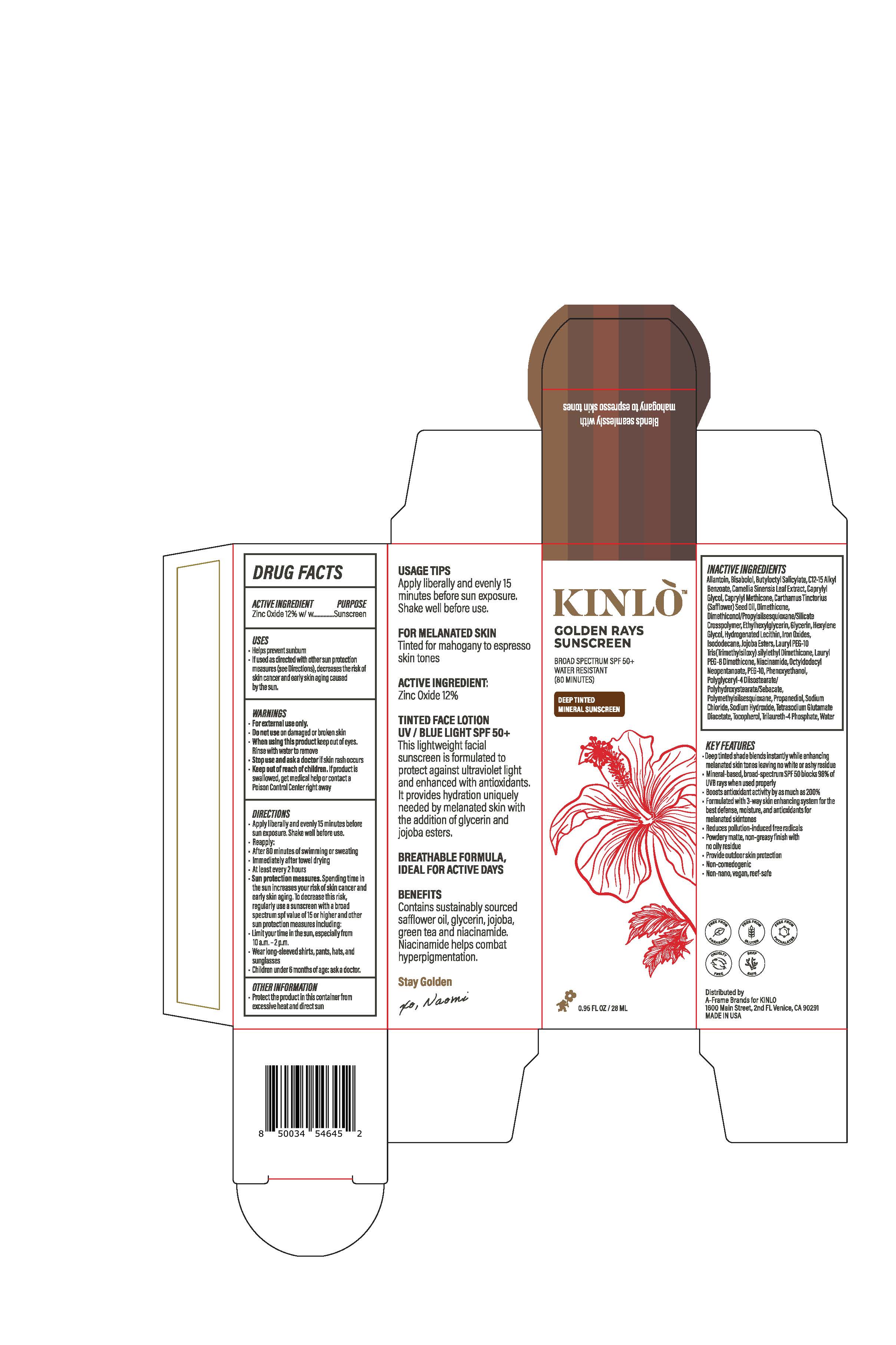 DRUG LABEL: Golden Ray Sunscreen (Deep Tinted)
NDC: 82184-1350 | Form: LOTION
Manufacturer: A-Frame SunCo Inc
Category: otc | Type: HUMAN OTC DRUG LABEL
Date: 20250109

ACTIVE INGREDIENTS: ZINC OXIDE 132 mg/1 mL
INACTIVE INGREDIENTS: FERRIC OXIDE RED; FERRIC OXIDE YELLOW; TOCOPHEROL; FERROSOFERRIC OXIDE; HYDROGENATED SOYBEAN LECITHIN; GLYCERIN; ALLANTOIN; ALKYL (C12-15) BENZOATE; DIMETHICONE; TRILAURETH-4 PHOSPHATE; BUTYLOCTYL SALICYLATE; OCTYLDODECYL NEOPENTANOATE; ISODODECANE; .ALPHA.-BISABOLOL, (+)-; SODIUM HYDROXIDE; WATER; NIACINAMIDE; ETHYLHEXYLGLYCERIN; HEXYLENE GLYCOL; DIMETHICONOL/PROPYLSILSESQUIOXANE/SILICATE CROSSPOLYMER (450000000 MW); PROPANEDIOL; TETRASODIUM GLUTAMATE DIACETATE; SODIUM CHLORIDE; PHENOXYETHANOL; POLYMETHYLSILSESQUIOXANE (4.5 MICRONS)

Golden Ray Sunscreen (Deep Tinted)